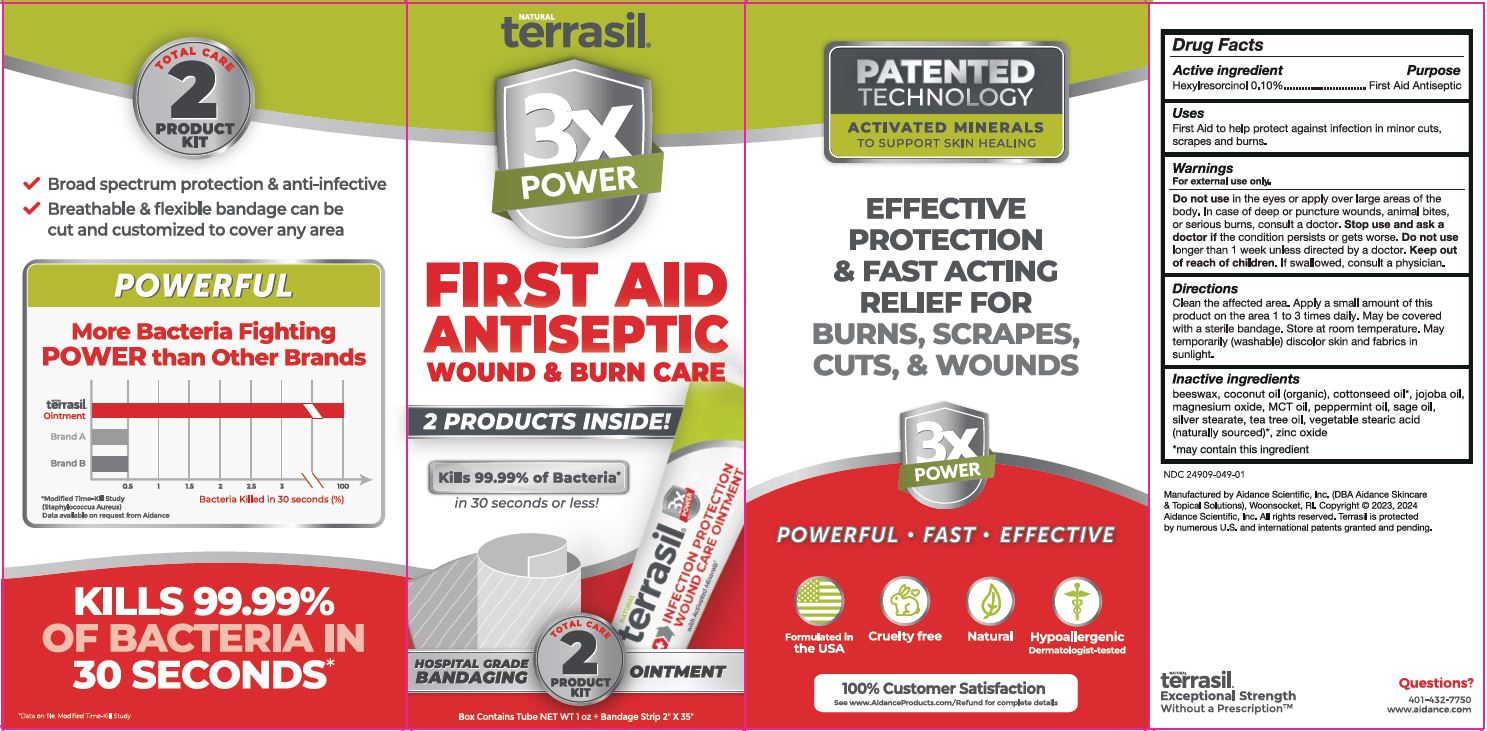 DRUG LABEL: terrasil First Aid Antiseptic Wound and Burn Care
NDC: 24909-049 | Form: KIT | Route: TOPICAL
Manufacturer: Aidance Scientific, Inc., DBA Aidance Skincare & Topical Solutions
Category: otc | Type: HUMAN OTC DRUG LABEL
Date: 20241226

ACTIVE INGREDIENTS: HEXYLRESORCINOL 0.1 g/100 g
INACTIVE INGREDIENTS: COCONUT OIL; SILVER STEARATE; MAGNESIUM OXIDE; PEPPERMINT OIL; YELLOW WAX; SAGE OIL; ZINC OXIDE; COTTONSEED OIL; PALM OIL; STEARIC ACID; TEA TREE OIL; JOJOBA OIL

24909-049 terrasil First Aid Antiseptic Kit

Active Ingredient

Hexylresorcinol 0.1%

Purpose

First Aid Antiseptic

Uses

First Aid to help protect against infection in minor cuts, scrapes and burns.

Warnings

For external use only.

.
Do not use in the eyes or apply over large areas of the body.

In case of deep or puncture wounds, animal bites, or serious burns, consult a doctor.

Stop use and ask a doctor if the condition persists or gets worse.

Do not use longer than 1 week unless directed by a doctor.

Keep out of reach of children.

OTHER SAFETY INFORMATION

If swallowed, consult a physician.

Directions

Clean the affected area. Apply a small amount of this product on the area 1 to 3 times daily. May be covered with a sterile bandage. Store at room temperature. May temporarily (washable) discolor skin and fabrics in sunlight.

Inactive ingredients

beeswax, coconut oil (organic), cottonseed oil*, jojoba oil, magnesium oxide, MCT oil, peppermint oil, sage oil, silver stearate, tea tree oil, vegetable stearic acid (naturally sourced)*, zinc oxide

*may contain this ingredient

Questions?

401-432-7750

www.aidance.com